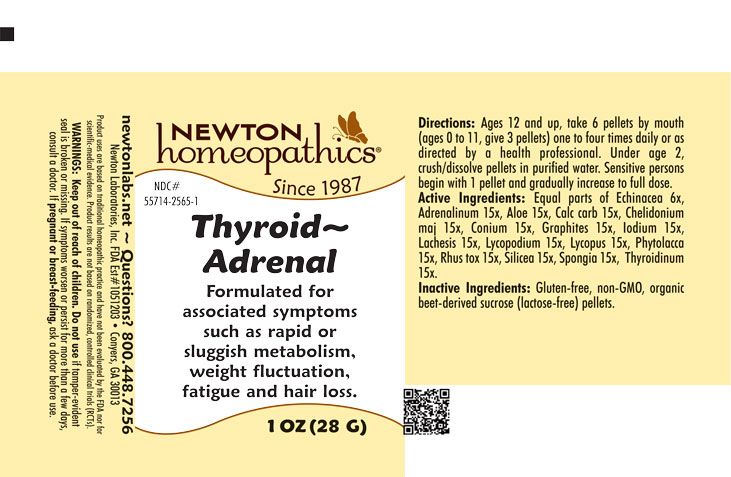 DRUG LABEL: Thyroid-Adrenal
NDC: 55714-2565 | Form: PELLET
Manufacturer: Newton Laboratories, Inc.
Category: homeopathic | Type: HUMAN OTC DRUG LABEL
Date: 20251125

ACTIVE INGREDIENTS: EPINEPHRINE 15 [hp_X]/1 g; THYROID, UNSPECIFIED 15 [hp_X]/1 g; ALOE 15 [hp_X]/1 g; OYSTER SHELL CALCIUM CARBONATE, CRUDE 15 [hp_X]/1 g; CHELIDONIUM MAJUS 15 [hp_X]/1 g; CONIUM MACULATUM FLOWERING TOP 15 [hp_X]/1 g; GRAPHITE 15 [hp_X]/1 g; IODINE 15 [hp_X]/1 g; LACHESIS MUTA VENOM 15 [hp_X]/1 g; LYCOPODIUM CLAVATUM SPORE 15 [hp_X]/1 g; LYCOPUS VIRGINICUS 15 [hp_X]/1 g; PHYTOLACCA AMERICANA ROOT 15 [hp_X]/1 g; TOXICODENDRON PUBESCENS LEAF 15 [hp_X]/1 g; SILICON DIOXIDE 15 [hp_X]/1 g; SPONGIA OFFICINALIS SKELETON, ROASTED 15 [hp_X]/1 g; ECHINACEA, UNSPECIFIED 6 [hp_X]/1 g
INACTIVE INGREDIENTS: SUCROSE

Thyroid 2565P

OTC - KEEP OUT OF REACH OF CHILDREN SECTION

Keep out of reach of children.

OTC - PREGNANCY OR BREAST FEEDING SECTION

If pregnant or breast-feeding, ask a doctor before use.

WARNINGS SECTION

WARNINGS: Keep out of reach of children. Do not use if tamper-evident seal is broken or missing. If symptoms worsen or persist for more than a few days, consult a doctor. If pregnant or breast-feeding, ask a doctor before use.

QUESTIONS SECTION

newtonlabs.net – Questions? 800.448.7256

Newton Laboratories, Inc. FDA Est # 1051203 - Conyers, GA 30013

INACTIVE INGREDIENT SECTION

Inactive Ingredients: Gluten-free, non-GMO, organic beet-derived sucrose (lactose-free) pellets.

OTC - PURPOSE SECTION

Formulated for associated symptoms such as rapid or sluggish metabolism, weight fluctuation, fatigue and hair loss.

OTC - ACTIVE INGREDIENT SECTION

Equal parts of Echinacea 6x, Aloe 10x, Calcarea carbonica 10x, Chelidonium majus 10x, Conium maculatum 10x, Graphites 10x, Iodium 10x, Lachesis mutus 10x, Lycopodium clavatum 10x, Lycopus virginicus 10x, Phytolacca decandra 10x, Rhus toxicodendron 10x, Silicea 10x, Spongia tosta 10x, Adrenalinum 15x, Thyroidinum 15x.

DOSAGE & ADMINISTRATION SECTION

Directions: Ages 12 and up, take 6 pellets by mouth (ages 0 to 11, give 3 pellets) one to four times daily or as directed by a health professional. Under age 2, crush/dissolve pellets in purified water. Sensitive persons begin with 1 pellet and gradually increase to full dose.

INDICATIONS & USAGE SECTION

Formulated for associated symptoms such as rapid or sluggish metabolism, weight fluctuation, fatigue and hair loss.